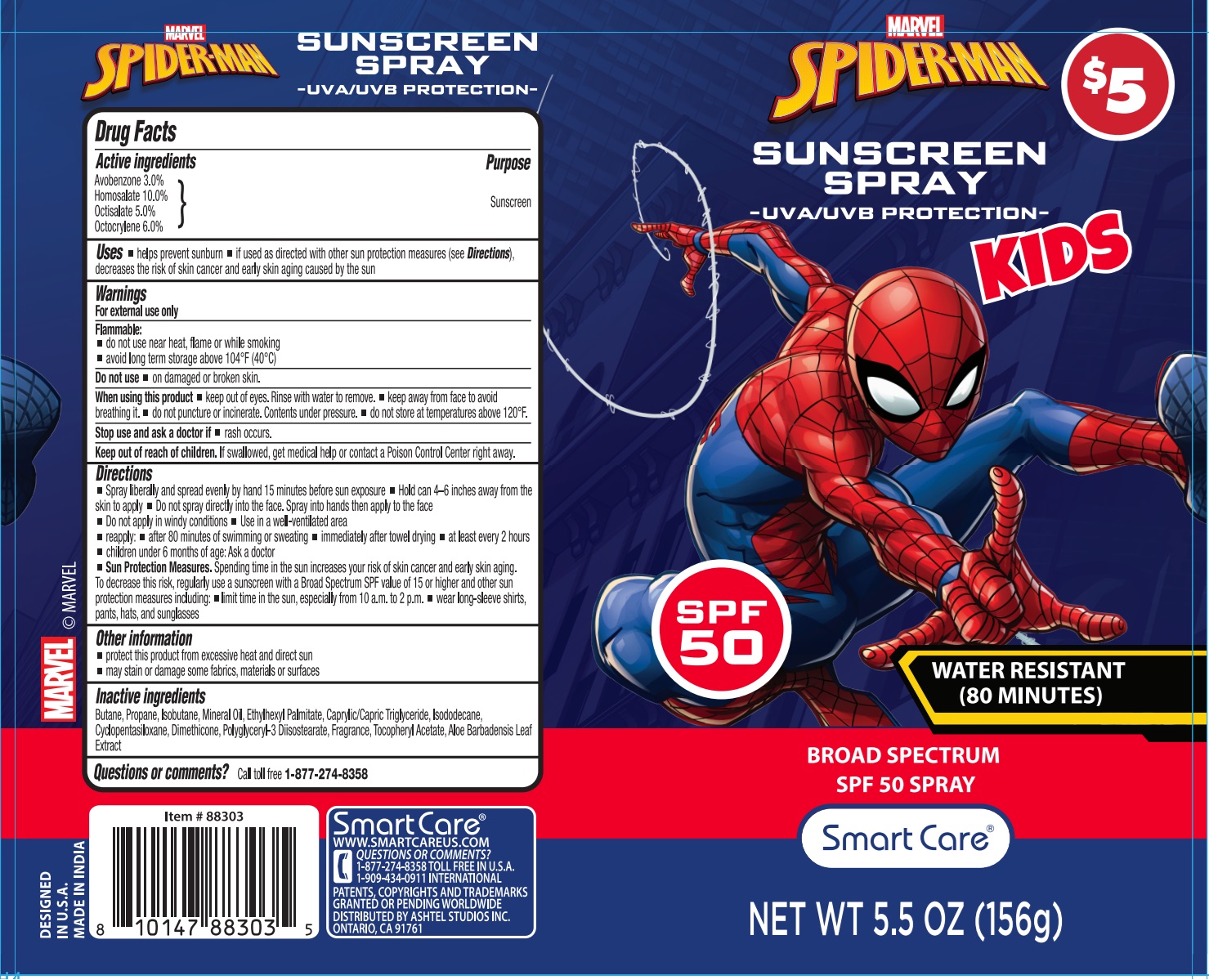 DRUG LABEL: Smart Care SPIDER-MAN KIDS SUNSCREEN SPF 50
NDC: 70108-114 | Form: SPRAY
Manufacturer: Ashtel Studios Inc.
Category: otc | Type: HUMAN OTC DRUG LABEL
Date: 20250213

ACTIVE INGREDIENTS: AVOBENZONE 3 g/100 g; HOMOSALATE 10 g/100 g; OCTISALATE 5 g/100 g; OCTOCRYLENE 6 g/100 g
INACTIVE INGREDIENTS: BUTANE; PROPANE; ISOBUTANE; MINERAL OIL; ETHYLHEXYL PALMITATE; MEDIUM-CHAIN TRIGLYCERIDES; ISODODECANE; CYCLOMETHICONE 5; DIMETHICONE, UNSPECIFIED; POLYGLYCERYL-3 DIISOSTEARATE; .ALPHA.-TOCOPHEROL ACETATE; ALOE VERA LEAF

Smart Care® SPIDER-MAN KIDS SUNSCREEN SPRAY

Active ingredients

Avobenzone 3.0%
Homosalate 10.0%
Octisalate 5.0%
Octocrylene 6.0%

Purpose

Sunscreen

Uses

• helps prevent sunburn • if used as directed with other sun protection measures (see Directions), decreases the risk of skin cancer and early skin aging caused by the sun

Warnings

For external use only

Flammable:
• do not use near heat, flame or while smoking
• avoid long term storage above 104°F (40°C)

Do not use • on damaged or broken skin.

When using this product • keep out of eyes. Rinse with water to remove. • keep away from face to avoid breathing it. • do not puncture or incinerate. Contents under pressure. • do not store at temperatures above 120°F.

Stop use and ask a doctor if • rash occurs.

Keep out of reach of children. If swallowed, get medical help or contact a Poison Control Center right away.

Directions

• Spray liberally and spread evenly by hand 15 minutes before sun exposure • Hold can 4-6 inches away from the skin to apply • Do not spray directly into the face. Spray into hands then apply to the face
• Do not apply in windy conditions • Use in a well-ventilated area
• reapply: • after 80 minutes of swimming or sweating • immediately after towel drying • at least every 2 hours
• children under 6 months of age: Ask a doctor
• Sun Protection Measures. Spending time in the sun increases your risk of skin cancer and early skin aging.
To decrease this risk, regularly use a sunscreen with a Broad Spectrum SPF value of 15 or higher and other sun protection measures including: • limit time in the sun, especially from 10 a.m. to 2 p.m. • wear long-sleeve shirts, pants, hats, and sunglasses

Other information

• protect this product from excessive heat and direct sun
• may stain or damage some fabrics, materials or surfaces

Inactive ingredients

Butane, Propane, Isobutane, Mineral Oil, Ethylhexyl Palmitate, Caprylic/Capric Triglyceride, Isododecane, Cyclopentasiloxane, Dimethicone, Polyglyceryl-3 Diisostearate, Fragrance, Tocopherol Acetate, Aloe Barbadensis Leaf Extract

Questions or comments?

Call toll free 1-877-274-8358

MARVEL

-UVA/UVB PROTECTION-

WATER RESISTANT (80 MINUTES)

WWW.SMARTCAREUS.COM
1-909-434-0911 INTERNATIONAL
PATENTS, COPYRIGHTS AND TRADEMARKS GRANTED OR PENDING WORLDWIDE
DISTRIBUTED BY ASHTEL STUDIOS INC.
ONTARIO, CA 91761

DESIGNED IN U.S.A.
MADE IN INDIA